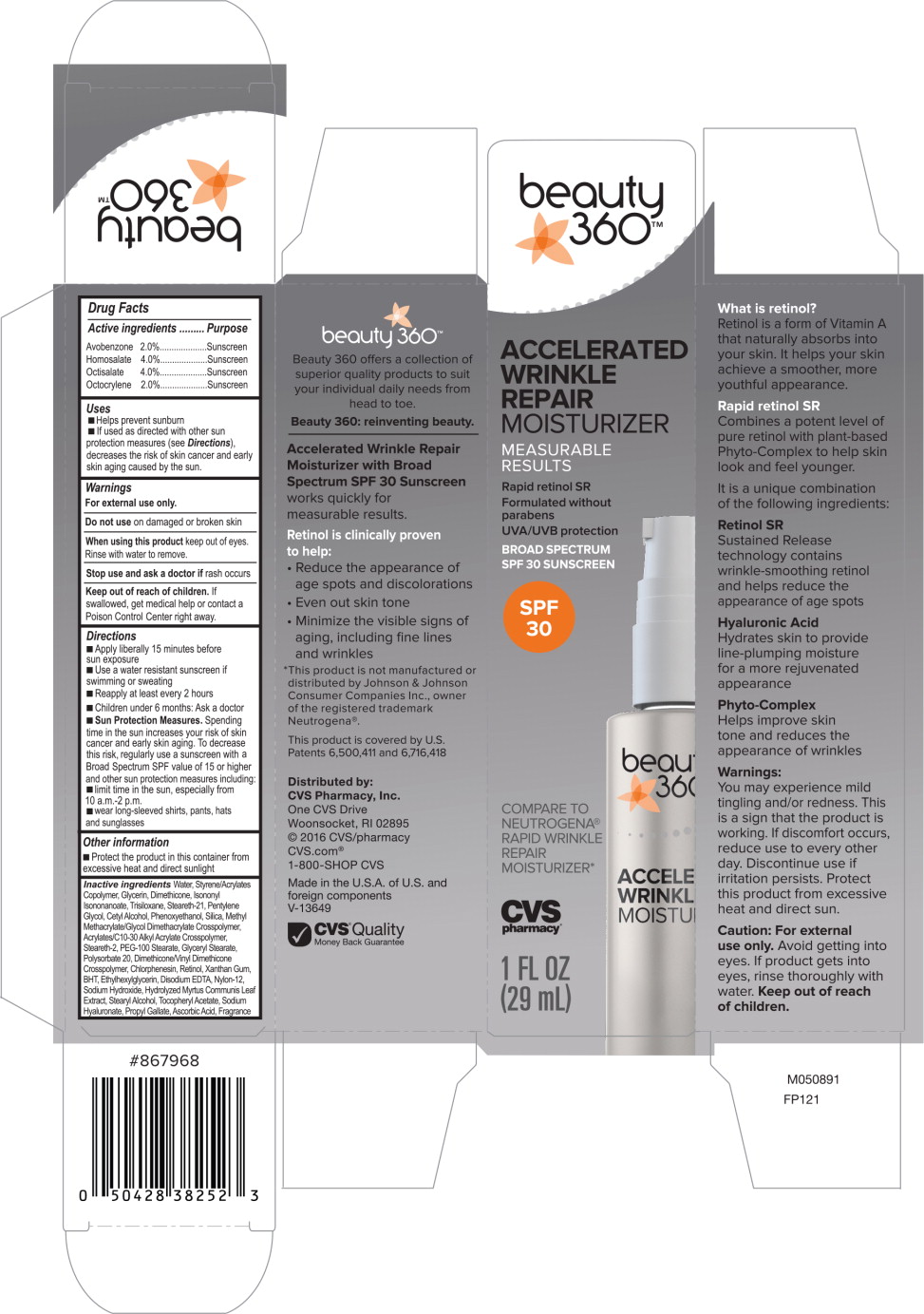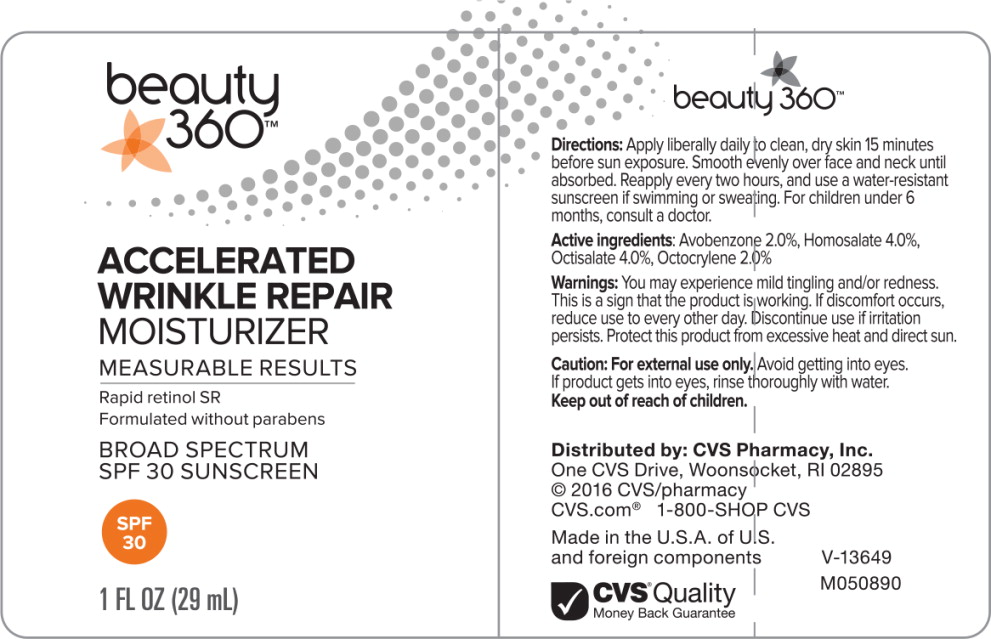 DRUG LABEL: Beauty 360 Accelerated Wrinkle Repair Moisturizer
NDC: 69842-080 | Form: LIQUID
Manufacturer: CVS Health
Category: otc | Type: HUMAN OTC DRUG LABEL
Date: 20170314

ACTIVE INGREDIENTS: homosalate 40 mg/1 mL; octisalate 40 mg/1 mL; avobenzone 20 mg/1 mL; octocrylene 20 mg/1 mL
INACTIVE INGREDIENTS: water; styrene/acrylamide copolymer (mw 500000); glycerin; dimethicone; isononyl Isononanoate; trisiloxane; steareth-21; pentylene glycol; cetyl alcohol; phenoxyethanol; silicon dioxide; methyl methacrylate/glycol dimethacrylate crosspolymer; carbomer copolymer type b (allyl pentaerythritol crosslinked); steareth-2; peg-100 stearate; glyceryl monostearate; polysorbate 20; dimethicone/vinyl dimethicone crosspolymer (soft particle); chlorphenesin; retinol; xanthan gum; butylated hydroxytoluene; ethylhexylglycerin; edetate disodium; nylon-12; sodium hydroxide; myrtus communis leaf; stearyl alcohol; .alpha.-tocopherol acetate; hyaluronate sodium; propyl Gallate; ascorbic acid

Drug Facts

Active ingredients

Avobenzone 2.0%

Homosalate 4.0%

Octisalate 4.0%

Octocrylene 2.0%

Purpose

Sunscreen

Sunscreen

Sunscreen

Sunscreen

Uses

- Helps prevent sunburn
- If used as directed with other sun protection measures (see Directions), decreases the risk of skin cancer and early skin aging cause by the sun.

Warnings

For external use only.

Do not use on damaged or broken skin

When using this product keep out of eyes. Rinse with water to remove.

Stop use and ask a doctor if rash occurs.

Keep out of reach of children. If swallowed, get medical help or contact a Poison Control Center right away.

Directions

- Apply liberally 15 minutes before sun exposure
- Use a water resistant sunscreen if swimming or sweating
- Reapply at least every 2 hours
- Children under 6 months: Ask a doctor
- Sun Protection Measures. Spending time in the sun increases your risk of skin cancer and early skin aging. To decrease this risk, regularly use a sunscreen with a Broad Spectrum SPF value of 15 or higher and other sun protection measures including:
- limit time in the sun, especially from 10 a.m.-2 p.m.
- wear long-sleeved shirts, pants, hats and sunglasses

Other information

- Protect the product in this container from excessive heat and direct sunlight

Inactive ingredients

Water, Styrene/Acrylates Copolymer, Glycerin, Dimethicone, Isononyl Isononanoate, Trisiloxane, Steareth-21, Pentylene Glycol, Cetyl Alcohol, Phenoxyethanol, Silica, Methyl Methacrylate/Glycol Dimethacrylate Crosspolymer, Acrylates/C10-30 Alkyl Acrylate Crosspolymer, Steareth-2, PEG-100 Stearate, Glyceryl Stearate, Polysorbate 20, Dimethicone/Vinyl Dimethicone Crosspolymer, Chlorphenesin, Retinol, Xanthan Gum, BHT, Ethylhexylglycerin, Disodium EDTA, Nylon-12, Sodium Hydroxide, Hydrolyzed Myrtus Communis Leaf Extract, Stearyl Alcohol, Tocopheryl Acetate, Sodium Hyaluronate, Propyl Gallate, Ascorbic Acid, Fragrance

Distributed by: CVS Pharmacy, Inc.

One CVS Drive, Woonsocket, RI 02895

© 2016 CVS/pharmacy

CVS.com® 1-800-SHOP CVS

Made in the U.S.A. of U.S. and foreign components

V-13649

CVS® Quality

Money Back Guarantee

M050891

FP121

Principal Display Panel - Carton Label

ACCELERATED
WRINKLE
REPAIR
MOISTURIZER

MEASURABLE
RESULTS

Rapid retinol SR

Formulated without
parabens

UVA/UVB protection

BROAD SPECTRUM
SPF 30 SUNSCREEN

SPF
30

COMPARE TO
NEUTROGENA®
RAPID WRINKLE
REPAIR
MOISTURIZER*

CVS
pharmacy®

1 FL OZ
(29 mL)

Principal Display Panel - Bottle Label

beauty
360™

ACCELERATED
WRINKLE
REPAIR
MOISTURIZER

MEASURABLE RESULTS

Rapid retinol SR

Formulated without parabens

BROAD SPECTRUM
SPF 30 SUNSCREEN

SPF
30

1 FL OZ (29 mL)